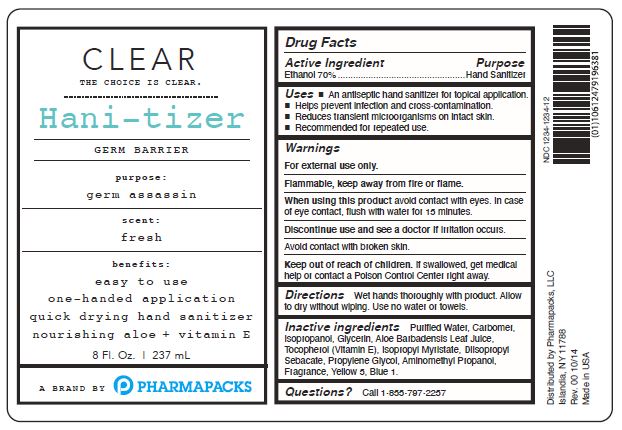 DRUG LABEL: CLEAR Hani-tizer
NDC: 73599-002 | Form: LIQUID
Manufacturer: PHARMAPACKS, LLC
Category: otc | Type: HUMAN OTC DRUG LABEL
Date: 20200305

ACTIVE INGREDIENTS: ALCOHOL 70 mL/100 mL
INACTIVE INGREDIENTS: DIISOPROPYL SEBACATE; WATER; CARBOMER HOMOPOLYMER, UNSPECIFIED TYPE; ISOPROPYL ALCOHOL; TOCOPHEROL; ISOPROPYL MYRISTATE; AMINOMETHYLPROPANOL; GLYCERIN; PROPYLENE GLYCOL; ALOE VERA LEAF; FD&C BLUE NO. 1

Active Ingredient

Ethanol 70%

Purpose

Hand Sanitizer

Uses

An antiseptic hand sanitizer for topical application.

Helps prevent infection and cross-contamination.

Reduces transient microorganisms on intact skin.

Recommended for repeated use.

Warnings

For external use only

Flammable, keep away from fire or flame.

When using this product avoid contact with eyes.

In case of eye contact, flush with water 15 minutes.

STOP USE

Discontinue use and see a doctor if irritation occurs.

Avoid contact with broken skin.

Keep out of reach of children.

If swallowed, get medical help or contact a Poison Control Center right away.

Directions

Wet hands thoroughly with product.

Allow to dry without wiping.

Use no water or towels.

Inactive ingredients

Purified Water, Carbomer, Isopropanol, Glycerin, Aloe Barbadensis Leaf Juice, Tocopherol (Vitamin E), Isopropyl Myristate, Diisopropyl Sebacate, Propylene Glycol, Aminomethyl Propanol, Fragrance, Yellow 5, Blue 1.

Questions?

Call 1-855-797-2257

PACKAGE LABEL

CLEAR

The Choice Is Clear

HANI-TIZER

Germ Barrier

purpose:

germ assassin

scent:

fresh

benefits:

easy to use

one-handed application

quick drying hand sanitizer

nourishing aloe + vitamin E

8 Fl.Oz. 237 mL

A Brand By PHARMAPACKS